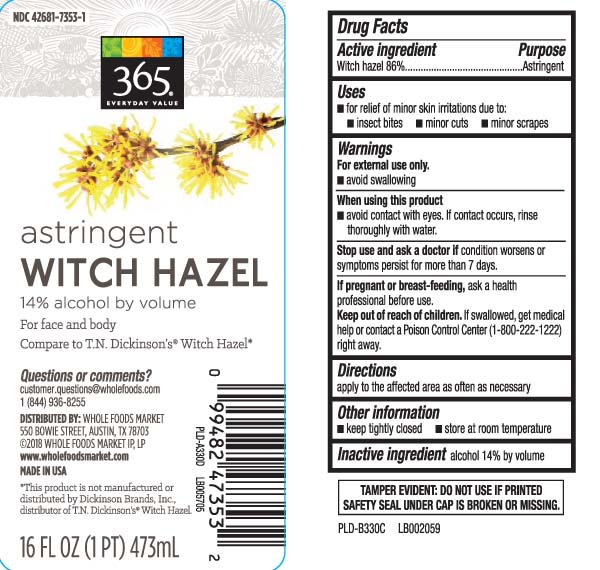 DRUG LABEL: Witch Hazel
NDC: 42681-7353 | Form: LIQUID
Manufacturer: Whole Foods Market
Category: otc | Type: HUMAN OTC DRUG LABEL
Date: 20250219

ACTIVE INGREDIENTS: WITCH HAZEL 842 mg/1 mL
INACTIVE INGREDIENTS: ALCOHOL

Drug Facts

Active ingredient

Witch hazel 86%

Purpose

Astringent

Uses

- for relief of minor skin irritations due to:
  - insect bites
  - minor cuts
  - minor scrapes

Warnings

- for external use only
- avoid swallowing

When using this product

- avoid contact with eyes. If contact occurs, rinse thoroughly with water.

Stop use and ask a doctor if

condition worsens or symptoms persist for more than 7 days.

If pregnant or breast-feeding,

ask a health professional before use.

Keep out of reach of children.

If swallowed, get medical help or contact a Poison Control Center (1-800-222-1222) right away.

Directions

apply to the affected area as often as necessary.

Other information

- keep tightly closed
- store at room temperature

Inactive ingredient

alcohol 14% by volume

Principal Display Panel

astringent

WITCH HAZEL

14% alcohol by volume

For Face and Body

Compare to T.N. Dickinson's® Witch Hazel*

Questions or comments?

customer, questions@wholefoods.com 1-844-936-8255

www.wholefoodsmarket.com

FL OZ (mL)

*This product is not manufactured or distributed by Dickinson Brands, Inc., distributor of T.N. Dickinson's® Witch Hazel

TAMPER EVIDENT: DO NOT USE IF PRINTED SAFETY SEAL UNDER CAP IS BROKEN OR MISSING.

DISTRIBUTED BY: WHOLE FOODS MARKET

550 BOWIE STREET, AUSTIN, TX 78703

Package Label

WHOLE FOOD Witch Hazel